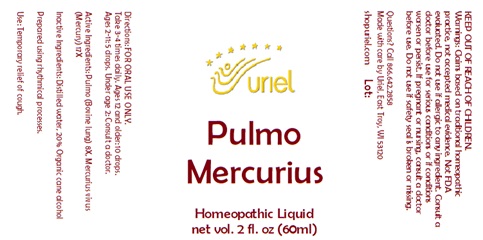 DRUG LABEL: Pulmo Mercurius
NDC: 48951-8425 | Form: LIQUID
Manufacturer: Uriel Pharmacy Inc.
Category: homeopathic | Type: HUMAN OTC DRUG LABEL
Date: 20251118

ACTIVE INGREDIENTS: SUS SCROFA LUNG 8 [hp_X]/1 mL; MERCURY 17 [hp_X]/1 mL
INACTIVE INGREDIENTS: ALCOHOL; WATER

Pulmo Mercurius

INDICATIONS AND USAGE

Directions: FOR ORAL USE ONLY.

DOSAGE AND ADMINISTRATION

Take 3-4 times daily. Ages 12 and older: 10 drops. Ages 2-11: 5 drops. Under age 2: Consult a doctor.

ACTIVE INGREDIENT

Active Ingredients: Pulmo (Bovine lung) 8X, Mercurius vivus (Mercury) 17X

Inactive Ingredients: Distilled water, 20% Organic cane alcohol

Prepared using rhythmical processes.

PURPOSE

Use: Temporary relief of cough.

KEEP OUT OF REACH OF CHILDREN.

WARNINGS

Warnings: Claims based on traditional homeopathic practice, not accepted medical evidence. Not FDA evaluated. Do not use if allergic to any ingredient. Consult a doctor before use for serious conditions or if conditions worsen or persist. If pregnant or nursing, consult a doctor before use. Do not use if safety seal is broken or missing.

QUESTIONS

Questions? Call 866.642.2858 Uriel, East Troy, WI 53120 shopuriel.com Lot: